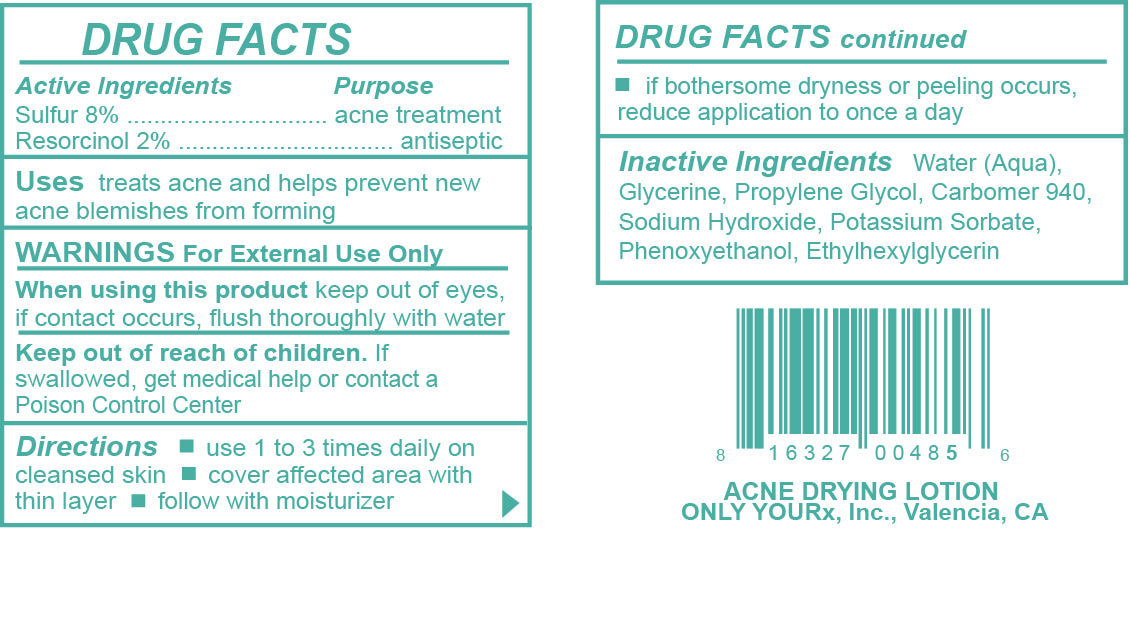 DRUG LABEL: Acne Drying Topical
NDC: 70367-012 | Form: LOTION
Manufacturer: Only Yourx, Inc.
Category: otc | Type: HUMAN OTC DRUG LABEL
Date: 20200123

ACTIVE INGREDIENTS: SULFUR 8 g/100 mL; RESORCINOL 2 g/100 mL
INACTIVE INGREDIENTS: GLYCERIN; SODIUM HYDROXIDE; POTASSIUM SORBATE; PHENOXYETHANOL; ETHYLHEXYLGLYCERIN; WATER; DIPROPYLENE GLYCOL; CARBOMER 934

ACTIVE INGREDIENT

Sulfur 8%, Resorcinol 2%

DOSAGE AND ADMINISTRATION

Use 1 to 3 times daily on cleansed skin; cover affected area with thin layer; follow with moisturizer

INDICATIONS AND USAGE

Treats acne and helps prevent new acne blemishes from forming

PURPOSE

Acne treatment and antiseptic

INACTIVE INGREDIENT

Water, Glycerine, Propylene Glycol, Carbomer 940, Sodium Hydroxide, Potassium Sorbate, Phenoxyethanl, Ethylhexylglycerin

WARNINGS

Warnings: For External Use Only; When using this product keep out of eyes, if contact occurs, flush thoroughly with water

Keep out of reach of children. If swallowed, get medical help or c.ontact a Poison Control Center.

OTHER SAFETY INFORMATION

If bothersome, dryness or peeling occurs, reduce application to once a day.